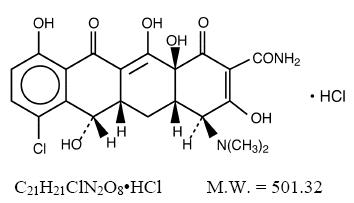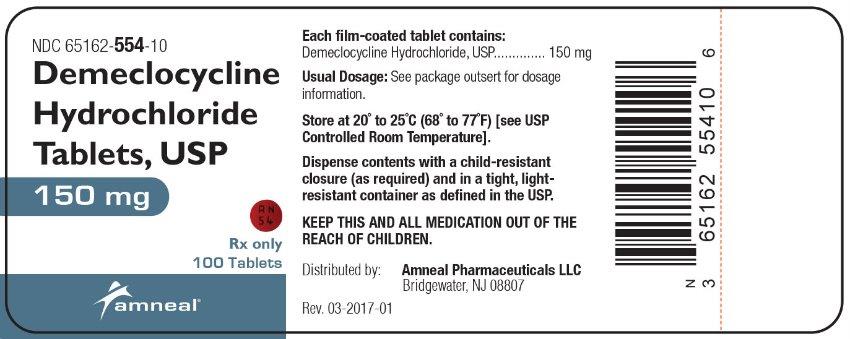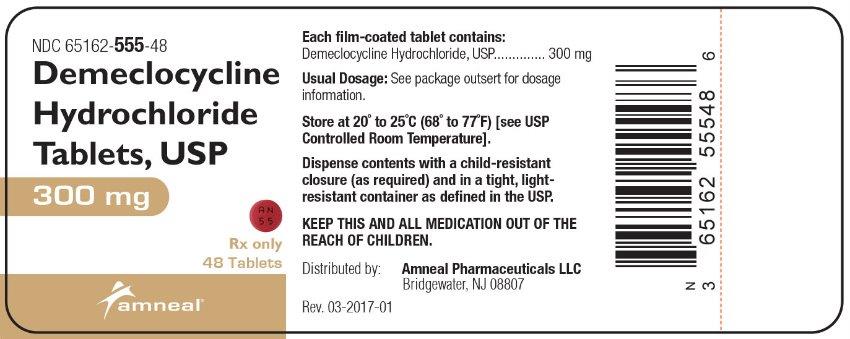 DRUG LABEL: Demeclocycline Hydrochloride
NDC: 65162-554 | Form: TABLET
Manufacturer: Amneal Pharmaceuticals LLC
Category: prescription | Type: HUMAN PRESCRIPTION DRUG LABEL
Date: 20241024

ACTIVE INGREDIENTS: DEMECLOCYCLINE HYDROCHLORIDE 150 mg/1 1
INACTIVE INGREDIENTS: ALGINIC ACID; STARCH, CORN; ETHYLCELLULOSES; FD&C RED NO. 40; HYPROMELLOSES; MAGNESIUM STEARATE; CELLULOSE, MICROCRYSTALLINE; POLYETHYLENE GLYCOL, UNSPECIFIED; POLYVINYL ALCOHOL, UNSPECIFIED; SODIUM LAURYL SULFATE; TALC; TITANIUM DIOXIDE; D&C RED NO. 27

DEMECLOCYCLINE HYDROCHLORIDE TABLETS, USP
FOR ORAL USE
RX ONLY
To reduce the development of drug-resistant bacteria and maintain the effectiveness of demeclocycline hydrochloride (HCl) tablets and other antibacterial drugs, demeclocycline HCl tablets should be used only to treat or prevent infections that are proven or strongly suspected to be caused by bacteria.

DESCRIPTION

Demeclocycline HCl is an antibiotic isolated from a mutant strain of Streptomyces aureofaciens. Chemically it is 7-Chloro-4-(dimethylamino)-1,4,4a,5,5a,6,11,12a-octahydro-3,6,10,12,12a-pentahydroxy-1,11-dioxo-2-naphthacenecarboxamide monohydrochloride.

Its structural formula is:

Demeclocycline HCl tablets, USP, for oral administration, contain 150 mg or 300 mg of demeclocycline HCl, USP and the following inactive ingredients: alginic acid, corn starch, ethylcellulose, FD&C Red 40 aluminum lake, hypromellose, magnesium stearate, microcrystalline cellulose, polyethylene glycol, polyvinyl alcohol, sodium lauryl sulfate, talc and titanium dioxide. In addition, the 150 mg tablet contains D&C Red 27 aluminum lake.

CLINICAL PHARMACOLOGY

Pharmacokinetics

The absorption of demeclocycline is slower than that of tetracycline. The time to reach the peak concentration is about 4 hours. After a 150 mg oral dose of demeclocycline tablet, the mean concentrations at 1 hour and 3 hours are 0.46 and 1.22 mcg/mL (n=6) respectively. The serum half-life ranges between 10 and 16 hours. When demeclocycline HCl is given concomitantly with some dairy products, or antacids containing aluminum, calcium, or magnesium, the extent of absorption is reduced by more than 50%. Demeclocycline HCl penetrates well into various body fluids and tissues. The percent of demeclocycline HCl bound to plasma protein is about 40% using a dialysis equilibrium method and 90% using an ultra-filtration method. Demeclocycline HCl, like other tetracyclines, is concentrated in the liver and excreted into the bile where it is found in much higher concentrations than in the blood. The rate of demeclocycline HCl renal clearance (35 mL/min/1.73 m^2) is less than half that of tetracycline. Following a single 150 mg dose of demeclocycline HCl in normal volunteers, 44% (n=8) was excreted in urine and 13% and 46%, respectively, were excreted in feces in two patients within 96 hours as active drug.

Microbiology

Mechanism of Action

The tetracyclines are primarily bacteriostatic and are thought to exert their antimicrobial effect by the inhibition of protein synthesis. The tetracyclines, including demeclocycline have a similar antimicrobial spectrum of activity against a wide range of gram-negative and gram-positive organisms.

Mechanism(s) of Resistance

Resistance to tetracyclines may be mediated by efflux, alteration in the target site of tetracycline, enzymatic inactivation, and decreased bacterial permeability to the tetracycline or a combination of these mechanisms.

Cross Resistance

Cross-resistance between antibiotics of the tetracycline family occurs.

Demeclocycline has been shown to be active against most isolates of the following bacteria, in vitro and/or in clinical infections as described in the INDICATIONS AND USAGE section.

Gram-positive bacteria

Bacillus anthracis

Listeria monocytogenes

Staphylococcus aureus

Streptococcus pneumoniae

Gram-negative bacteria

Bartonella bacilliformis

Brucella species

Calymmatobacterium granulomatis

Campylobacter fetus

Francisella tularensis

Haemophilus ducreyi

Haemophilus influenzae

Neisseria gonorrhoeae

Vibrio cholerae

Yersinia pestis

Because isolates of the following groups of gram-negative bacteria have been shown to be resistant to tetracyclines, culture and susceptibility testing are especially recommended:

Acinetobacter species

Enterobacter aerogenes

Escherichia coli

Klebsiella species

Shigella species

Other microorganisms

Actinomyces israelii

Borrelia recurrentis

Chlamydia psittaci

Chlamydia trachomatis

Clostridium species

Entamoeba species

Fusobacterium fusiforme

Mycoplasma pneumoniae

Propionibacterium acnes

Rickettsiae

Treponema pallidum subspecies pallidum

Treponema pallidum subspecies pertenue

Ureaplasma urealyticum

Susceptibility Test Methods

For specific information regarding susceptibility test interpretive criteria and associated test methods and quality control standards recognized by FDA for this drug, please see: https://www.fda.gov/STIC.

INDICATIONS AND USAGE

Demeclocycline HCl tablets are indicated in the treatment of infections caused by susceptible strains of the designated microorganisms in the conditions below:

Rocky Mountain spotted fever, typhus fever and the typhus group, Q fever, rickettsialpox and tick fevers caused by rickettsiae;

Respiratory tract infections caused by Mycoplasma pneumoniae

Lymphogranuloma venereum due to Chlamydia trachomatis

Psittacosis (Ornithosis) due to Chlamydia psittaci

Trachoma due to Chlamydia trachomatis, although the infectious agent is not always eliminated as judged by immunofluorescence

Inclusion conjunctivitis caused by Chlamydia trachomatis

Nongonococcal urethritis in adults caused by Ureaplasma urealyticum or Chlamydia trachomatis

Relapsing fever due to Borrelia recurrentis

Chancroid caused by Haemophilus ducreyi

Plague due to Yersinia pestis

Tularemia due to Francisella tularensis

Cholera caused by Vibrio cholerae

Campylobacter fetus infections cause by Campylobacter fetus

Brucellosis due to Brucella species (in conjunction with streptomycin);

Bartonellosis due to Bartonella bacilliformis

Granuloma inguinale caused by Calymmatobacterium granulomatis

Demeclocycline HCl tablets are indicated for treatment of infections by the following gram-negative microorganisms, when bacteriologic testing indicates appropriate susceptibility to the drug:

Escherichia coli

Enterobacter aerogenes

Shigella species

Acinetobacter species

Respiratory tract infections caused by Haemophilus influenzae

Respiratory tract and urinary tract infections caused by Klebsiella species

Demeclocycline HCl tablets are indicated for treatment of infections caused by the following gram-positive microorganisms, when bacteriologic testing indicates appropriate susceptibility to the drug:

Upper respiratory infections caused by Streptococcus pneumoniae

Skin and skin structure infections caused by Staphylococcus aureus. (Note: Tetracyclines, including demeclocycline, are not the drugs of choice in the treatment of any type of staphylococcal infection).

When penicillin is contraindicated, tetracyclines, including demeclocycline HCl, are alternative drugs in the treatment of the following infections:

Uncomplicated urethritis in men due to Neisseria gonorrhoeae, and for the treatment of other uncomplicated gonococcal infections

Infections in women caused by Neisseria gonorrhoeae

Syphilis caused by Treponema pallidum subspecies pallidum

Yaws caused by Treponema pallidum subspecies pertenue

Listeriosis due to Listeria monocytogenes

Anthrax due to Bacillus anthracis

Vincent’s infection caused by Fusobacterium fusiforme

Actinomycosis caused by Actinomyces israelii

Clostridial diseases caused by Clostridium species

In acute intestinal amebiasis, demeclocycline HCl may be a useful adjunct to amebicides.

In severe acne, demeclocycline HCl may be a useful adjunctive therapy.

To reduce the development of drug-resistant bacteria and maintain the effectiveness of demeclocycline HCl tablets and other antibacterial drugs, demeclocycline HCl tablets should be used only to treat or prevent infections that are proven or strongly suspected to be caused by susceptible bacteria. When culture and susceptibility information are available they should be considered in selecting or modifying antibacterial therapy. In the absence of such data, local epidemiology and susceptibility patterns may contribute to the empiric selection of therapy.

CONTRAINDICATIONS

This drug is contraindicated in persons who have shown hypersensitivity to any of the tetracyclines or any of the components of the product formulation.

WARNINGS

DEMECLOCYCLINE HCl, LIKE OTHER TETRACYCLINE-CLASS ANTIBIOTICS, CAN CAUSE FETAL HARM WHEN ADMINISTERED TO A PREGNANT WOMAN. IF ANY TETRACYCLINE IS USED DURING PREGNANCY, OR IF THE PATIENT BECOMES PREGNANT WHILE TAKING THESE DRUGS, THE PATIENT SHOULD BE APPRISED OF THE POTENTIAL HAZARD TO THE FETUS.

THE USE OF DRUGS OF THE TETRACYCLINE CLASS DURING TOOTH DEVELOPMENT (LAST HALF OF PREGNANCY INFANCY AND CHILDHOOD TO THE AGE OF 8 YEARS) MAY CAUSE PERMANENT DISCOLORATION OF THE TEETH (YELLOW-GRAY-BROWN). This adverse reaction is more common during long-term use of the drugs but has been observed following repeated short-term courses. Enamel hypoplasia has also been reported. TETRACYCLINE DRUGS, THEREFORE, SHOULD NOT BE USED DURING TOOTH DEVELOPMENT UNLESS OTHER DRUGS ARE NOT LIKELY TO BE EFFECTIVE OR ARE CONTRAINDICATED.

All tetracyclines form a stable calcium complex in any bone-forming tissue. A decrease in fibula growth rate has been observed in premature human infants given oral tetracycline in doses of 25 mg/kg/ every six hours. This reaction was shown to be reversible when the drug was discontinued.

Results of animal studies indicate that tetracyclines cross the placenta, are found in fetal tissues, and can have toxic effects on the developing fetus (often related to retardation of skeletal development). Evidence of embryotoxicity has also been noted in animals treated early in pregnancy. The anti-anabolic action of the tetracyclines may cause an increase in BUN. While this is not a problem in those with normal renal function, in patients with significantly impaired function, higher serum levels of tetracycline may lead to azotemia, hyperphosphatemia and acidosis. If renal impairment exists, even usual oral or parenteral doses may lead to excessive systemic accumulation of the drug and possible liver toxicity. Under such conditions, lower than usual total doses are indicated and, if therapy is prolonged, serum level determinations of the drug may be advisable.

Photosensitivity manifested by an exaggerated sunburn reaction has been observed in some individuals taking tetracyclines. Phototoxic reactions can occur in individuals taking demeclocycline, and are characterized by severe burns or exposed surfaces resulting from direct exposure of patients to sunlight during therapy with moderate or large doses of demeclocycline. Patients apt to be exposed to direct sunlight or ultraviolet light should be advised that this reaction can occur and treatment should be discontinued at the first evidence of erythema of the skin.

Administration of demeclocycline HCl has resulted in appearance of the diabetes insipidus syndrome (polyuria, polydipsia and weakness) in some patients on long-term therapy. The syndrome has been shown to be nephrogenic, dose-dependent and reversible on discontinuance of therapy. Patients, who are experiencing central nervous system symptoms associated with demeclocycline therapy, should be cautioned about driving vehicles or using hazardous machinery while on demeclocycline therapy.

Clostridium difficile associated with diarrhea (CDAD) has been reported with use of nearly all antibacterial agents, including demeclocycline HCl and may range in severity from mild diarrhea to fatal colitis. Treatment with antibacterial agents alters the normal flora of the colon leading to overgrowth of C. difficile.

C. difficile produces toxins A and B which contribute to the development of CDAD. Hypertoxin producing strains of C. difficile cause increased morbidity and mortality, as these infections can be refractory to antimicrobial therapy and may require colectomy. CDAD must be considered in all patients who present with diarrhea following antibiotic use. Careful medical history is necessary since CDAD has been reported to occur over two months after the administration of antibacterial agents.

If CDAD is suspected or confirmed, ongoing antibiotic use not directed against C. difficile may need to discontinue. Appropriate fluid and electrolyte management, protein supplementation, antibiotic treatment of C. difficile, and surgical evaluation should be instituted as clinically indicated.

PRECAUTIONS

General

Pseudotumor cerebri (benign intracranial hypertension) in adults has been associated with the use of tetracyclines. The usual clinical manifestations are headache and blurred vision. Bulging fontanels have been associated with the use of tetracyclines in infants. While both of these conditions and related symptoms usually resolve soon after discontinuation of the tetracycline, the possibility for permanent sequelae exists.

As with other antibiotic preparations, use of this drug may result in overgrowth of nonsusceptible organisms, including fungi. If superinfection occurs, the antibiotic should be discontinued and appropriate therapy should be instituted. Incision and drainage or other surgical procedures should be performed in conjunction with antibiotic therapy, when indicated. Prescribing demeclocycline HCl tablets in the absence of a proven or strongly suspected bacterial infection or a prophylactic indication is unlikely to provide benefit to the patient and increases the risk of the development of drug-resistant bacteria.

Information for Patients

Photosensitivity manifested by an exaggerated sunburn reaction has been observed in some individuals taking tetracyclines. Patients apt to be exposed to direct sunlight or ultraviolet light should be advised that this reaction can occur with tetracycline drugs, and treatment should be discontinued at the first evidence of skin erythema. Concurrent use of tetracyclines with oral contraceptives may render oral contraceptives less effective (see Drug Interactions). Patients should be informed that demeclocycline HCl tablets should be taken at least 1 hour before meals or 2 hours after meals (see DOSAGE AND ADMINISTRATION). Unused supplies of tetracycline antibiotics should be discarded by the expiration date. Patients who are experiencing headache, dizziness, light-headedness, vertigo, or blurred vision while on demeclocycline therapy, should be cautioned about driving vehicles or using hazardous machinery while receiving demeclocycline therapy (see WARNINGS).

Patients should be counseled that antibacterial drugs, including demeclocycline HCl tablets, should only be used to treat bacterial infections. They do not treat viral infections (e.g., the common cold). When demeclocycline HCl tablets are prescribed to treat a bacterial infection, patients should be told that although it is common to feel better early in the course of therapy, the medication should be taken exactly as directed.

Skipping doses or not completing the full course of therapy may (1) decrease the effectiveness of the immediate treatment and (2) increase the likelihood that bacteria will develop resistance and will not be treatable by demeclocycline HCl tablets or other antibacterial drugs in the future.

Diarrhea is a common problem caused by antibiotics which usually ends when the antibiotic is discontinued. Sometimes after starting treatment with antibiotics, patients can develop watery and bloody stools (with or without stomach cramps and fever) even as late as two or more months after having taken the last dose of the antibiotic. If this occurs, patients should contact their physician as soon as possible.

Laboratory Tests

In venereal diseases when coexistent syphilis is suspected, darkfield examination should be done before treatment is started and the blood serology repeated monthly for at least 4 months. In long-term therapy, periodic laboratory evaluation of organ systems, including hematopoietic, renal and hepatic, should be performed. All patients with gonorrhea should have a serologic test for syphilis at the time of diagnosis. Patients treated with demeclocycline HCl should have a follow-up serologic test for syphilis after 3 months.

Drug Interactions

Because tetracyclines have shown to depress plasma prothrombin activity, patients who are on anticoagulant therapy may require downward adjustment of their anticoagulant dosage. Since bacteriostatic drugs may interfere with the bactericidal action of penicillins, it is advisable to avoid giving tetracycline-class drugs in conjunction with penicillin.

Concurrent use of tetracyclines with oral contraceptives may render oral contraceptives less effective.

The concurrent use of tetracyclines and methoxyflurane has been reported to result in fatal renal toxicity.

Absorption of tetracyclines is impaired by antacids containing aluminum, calcium or magnesium and by iron-containing preparations.

Carcinogenesis, Mutagenesis, Impairment of Fertility

Long-term studies in animals to evaluate carcinogenic potential of demeclocycline HCl have not been conducted. However, there has been evidence of oncogenic activity in rats in studies with the related antibiotics oxytetracycline (adrenal and pituitary tumors) and minocycline (thyroid tumors).

Although mutagenicity studies of demeclocycline HCl have not been conducted, positive results in in vitro mammalian cell assays (i.e., mouse lymphoma and Chinese hamster lung cells) have been reported for related antibiotics (tetracyclines HCl and oxytetracycline) (see WARNINGS and ANIMAL PHARMACOLOGY AND ANIMAL TOXICOLOGY).

Demeclocycline HCl had no effect on fertility when administered in the diet to male and female rats at a daily intake of 45 times the human dose.

Pregnancy

Teratogenic effects

Pregnancy Category D

(See WARNINGS). Result of animal studies indicate that tetracyclines cross the placenta, are found in fetal tissues, and can have toxic effects on the developing fetus (often related to retardation of skeletal development). Evidence of embryotoxicity has been noted in animals treated early in pregnancy.

Nonteratogenic effects

(See WARNINGS)

Labor and Delivery

The effect of tetracyclines on labor and delivery is unknown.

Nursing Mothers

Tetracyclines are excreted in human milk. Because of the potential for serious adverse reactions in nursing infants from the tetracyclines, a decision should be made whether to discontinue nursing or discontinue the drug, taking into account the importance of the drug to the mother (see WARNINGS).

Pediatric Use

Not for use in patients younger than eight years of age [see WARNINGS, PRECAUTIONS (General subsection) and DOSAGE AND ADMINISTRATION].

ADVERSE REACTIONS

The following reactions have been reported in patients receiving tetracyclines:

Gastrointestinal: Anorexia, nausea, vomiting, diarrhea, glossitis, dysphagia, enterocolitis, pancreatitis and inflammatory lesions (with monilial overgrowth) in the anogenital region, increases in liver enzymes, and hepatic toxicity has been reported rarely.

Rarely, hepatitis and liver failure have been reported. These reactions have been caused by both the oral and parenteral administration of tetracyclines.

Instances of esophageal ulcerations have been reported in patients receiving oral tetracyclines. Most of the patients were reported to have taken the medication immediately before lying down (see DOSAGE AND ADMINISTRATION).

Skin: Maculopapular and erythematous rashes, erythema multiforme. Exfoliative dermatitis has been reported but is uncommon. Fixed drug eruptions and Stevens-Johnson syndrome have been reported rarely. Lesions occurring on the glans penis have caused balanitis. Pigmentation of the skin and mucous membranes has also been reported. Photosensitivity is discussed above (see WARNINGS).

Renal toxicity: Acute renal failure, rise in BUN has been reported and is apparently dose related, nephrogenic diabetes insipidus (see WARNINGS).

Hypersensitivity reactions: Urticaria, angioneurotic edema, polyarthralgia, anaphylaxis, anaphylactoid purpura, pericarditis exacerbation of systemic lupus erythematosus, lupus-like syndrome, pulmonary infiltrates with eosinophilia.

Hematologic: Hemolytic anemia, thrombocytopenia, neutropenia and eosinophilia have been reported.

CNS: Pseudotumor cerebri (benign intracranial hypertension) in adults and bulging fontanels in infants (see PRECAUTIONS – General). Dizziness, headache, tinnitus and visual disturbances have been reported. Myasthenic syndrome has been reported rarely.

Other: When given over prolonged periods, tetracyclines have been reported to produce brown-black microscopic discoloration of thyroid glands. No abnormalities of thyroid function studies are known to occur. Very rare cases of abnormal thyroid function have been reported.

Tooth discoloration has occurred in pediatric patients less than 8 years of age (see WARNINGS), and has been reported rarely in adults.

To report SUSPECTED ADVERSE REACTIONS, contact Amneal Pharmaceuticals at 1-877-835-5472 or FDA at 1-800-FDA-1088 or www.fda.gov/medwatch.

OVERDOSAGE

In case of overdosage, discontinue medication, treat symptomatically and institute supportive measures. Tetracyclines are not removed in significant quantities by hemodialysis or peritoneal dialysis.

DOSAGE AND ADMINISTRATION

Therapy should be continued for at least 24 to 48 hours after symptoms and fever have subsided.

Concomitant therapy: Absorption of tetracyclines is impaired by antacids containing aluminum, calcium, or magnesium and by iron-containing preparations. Foods and some dairy products also interfere with absorption. Oral forms of tetracycline should be given at least 1 hour before or 2 hours after meals.

In patients with renal impairment: (see WARNINGS). Tetracyclines should be used cautiously in patients with impaired renal function. Total dosage should be decreased by reduction of recommended individual doses and/or by extending time intervals between doses.

In patients with liver impairment: Tetracyclines should be used cautiously in patients with impaired liver function. Total dosage should be decreased by reduction of recommended individual doses and/or by extending time intervals between doses. Administration of adequate amounts of fluid with the oral formulations of tetracyclines is recommended to wash down the drugs and reduce the risk of esophageal irritation and ulceration (see ADVERSE REACTIONS).

Adults: Usual daily dose – Four divided doses of 150 mg each or two divided doses of 300 mg each.

For pediatric patients above eight years of age: Usual daily dose, 7 to 13 mg per kg body weight per day, depending upon the severity of the disease, divided into two to four doses not to exceed adult dosage of 600 mg per day.

Gonorrhea patients sensitive to penicillin may be treated with demeclocycline administered as an initial oral dose of 600 mg followed by 300 mg every 12 hours for four days to a total of 3 grams.

HOW SUPPLIED

Demeclocycline HCl tablets, USP, 150 mg, are supplied as round, convex, red, film-coated tablets, debossed with “AN” above “54” on one side and plain on the other side.
They are available as follows:

Bottles of 100: NDC 65162-554-10

Demeclocycline HCl tablets, USP, 300 mg, are supplied as round, convex, red, film-coated tablets, debossed with “AN” above “55” on one side and plain on the other side.
They are available as follows:

Bottles of 48: NDC 65162-555-48

Store at 20° to 25°C (68° to 77°F) [see USP Controlled Room Temperature].

Dispense in a tight container as defined in the USP. Protect from light.

KEEP THIS AND ALL DRUGS OUT OF THE REACH OF CHILDREN.

ANIMAL PHARMACOLOGY AND ANIMAL TOXICOLOGY

Hyperpigmentation of the thyroid has been produced by members of the tetracycline class in the following species: in rats by oxytetracycline, doxycycline, tetracycline PO4 and methacycline; in minipigs by doxycycline, minocycline, tetracycline PO4 and methacycline; in dogs by doxycycline and minocycline; in monkeys by minocycline.

Minocycline, tetracycline PO4, methacycline, doxycycline, tetracycline base oxytetracycline HCl and tetracycline HCl, were goitrogenic in rats fed a low iodine diet. This goitrogenic effect was accompanied by high radioactive iodine uptake. Administration of minocycline also produced a large goiter with high radioiodine uptake in rats fed a relatively high iodine diet.

Treatment of various animal species with this class of drugs has also resulted in the induction of thyroid hyperplasia in the following: in rats and dogs (minocycline), in chickens (chlortetracycline) and in rats and mice (oxytetracycline). Adrenal gland hyperplasia has been observed in goats and rats treated with oxytetracycline.

Distributed by:

Amneal Pharmaceuticals LLC

Bridgewater, NJ 08807

Rev. 05-2018-03